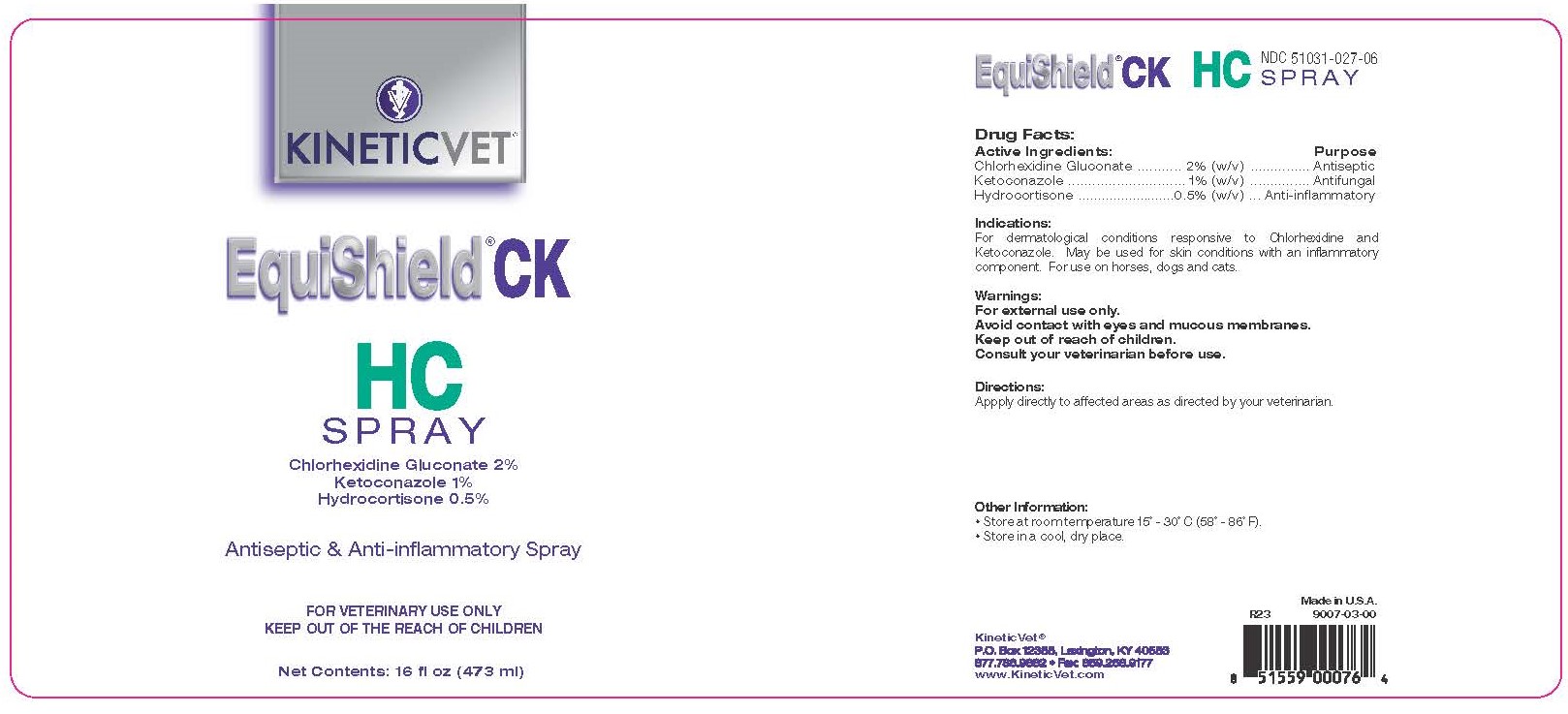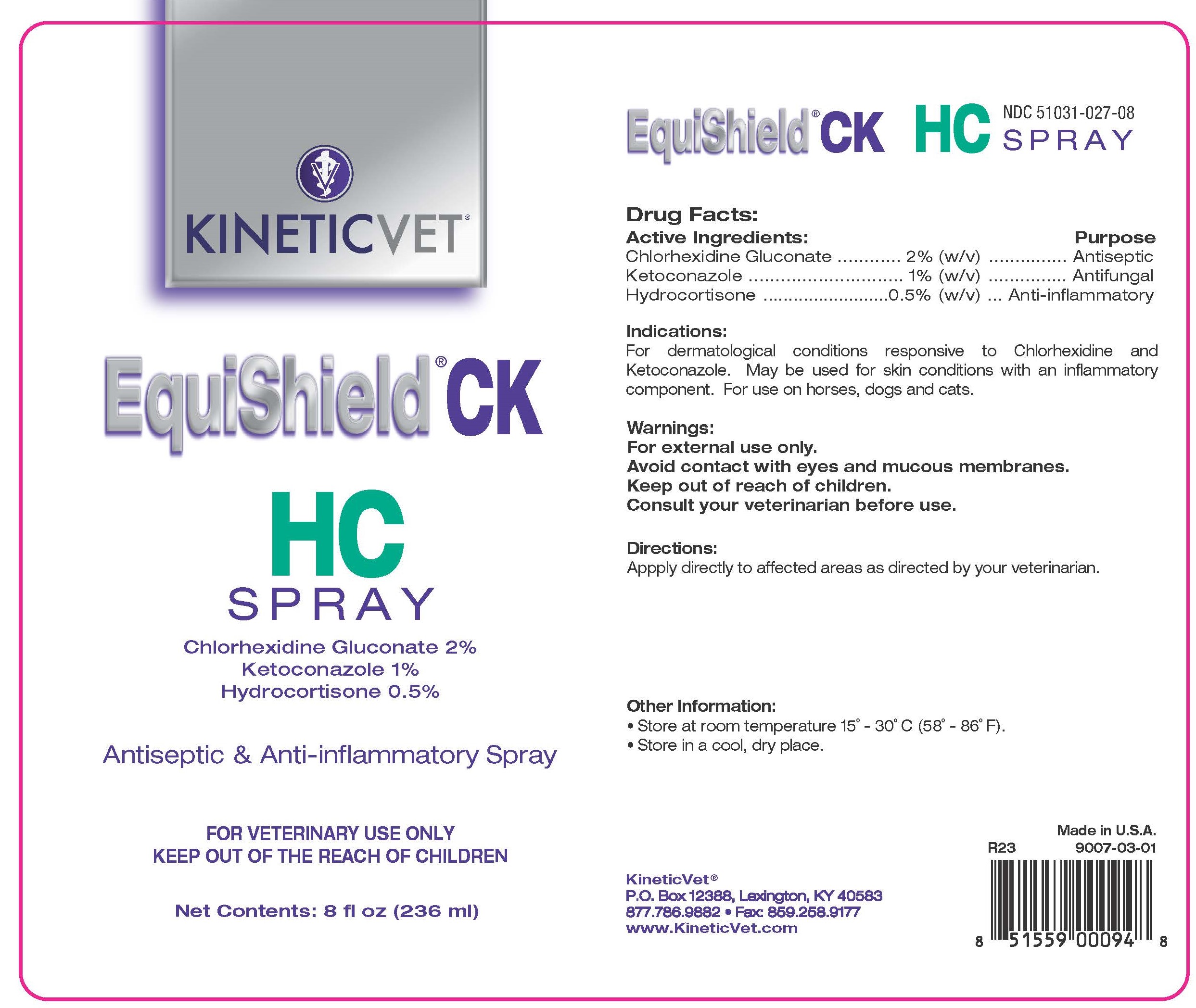 DRUG LABEL: EquiShield CK HC
NDC: 51031-027 | Form: SPRAY
Manufacturer: Kinetic Technologies, LLC
Category: animal | Type: OTC ANIMAL DRUG LABEL
Date: 20230828

ACTIVE INGREDIENTS: CHLORHEXIDINE GLUCONATE 20 mg/1 mL; KETOCONAZOLE 10 mg/1 mL; HYDROCORTISONE 5 mg/1 mL

EquiShield CK HC SPRAY

Active Ingredients:

Chlorhexidine Gluconate ........... 2% (w/v)......................Antiseptic
Ketoconazole ........................... 1% (w/v).....................Antifungal
Hydrocortisone ...................... 0.5% (w/v)........Anti-inflammatory

Indications:

For dermatological conditions responsive to Chlorhexidine and Ketoconazole. May be used for skin conditions with an inflammatory component. For use on horses, dogs and cats.

Warnings:

For external use only.
Avoid contact with eyes and mucous membranes.
Keep out of reach of children.
Consult your veterinarian before use.

Directions:

Apply directly to affected areas as directed by your veterinarian.

Other Information:

• Store at room temperature 15˚ - 30˚C (58˚ - 86˚F).
• Store in a cool, dry place.

NDC 51031-027-08

NDC 51031-027-06

Made in U.S.A.

#9007-03-01

#9007-03-00

KINETIC™

P.O. Box 12388, Lexington, KY 40583

877.786.9882 • Fax: 859.258.9177

www.KineticVet.com

KINETICVET®

EquiShield® CK HC SPRAY

Chlorhexidine Gluconate 2%

Ketoconazole 1%

Hydrocortisone 0.5%

Antisptic & Anti-inflammatory Spray

FOR VETERINARY USE ONLY

KEEP OUT OF THE REACH OF CHILDREN

Net Contents: 8 fl oz (236 ml)

Net Contents: 16 fl oz (473 ml)